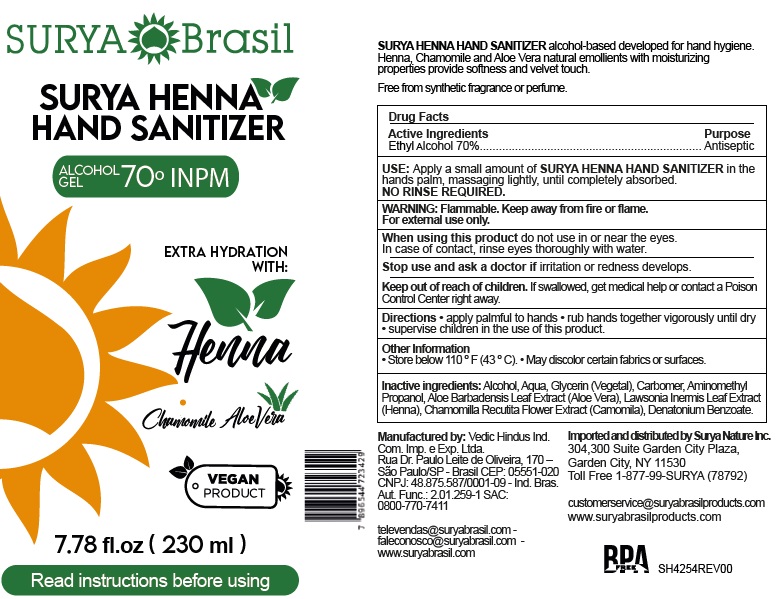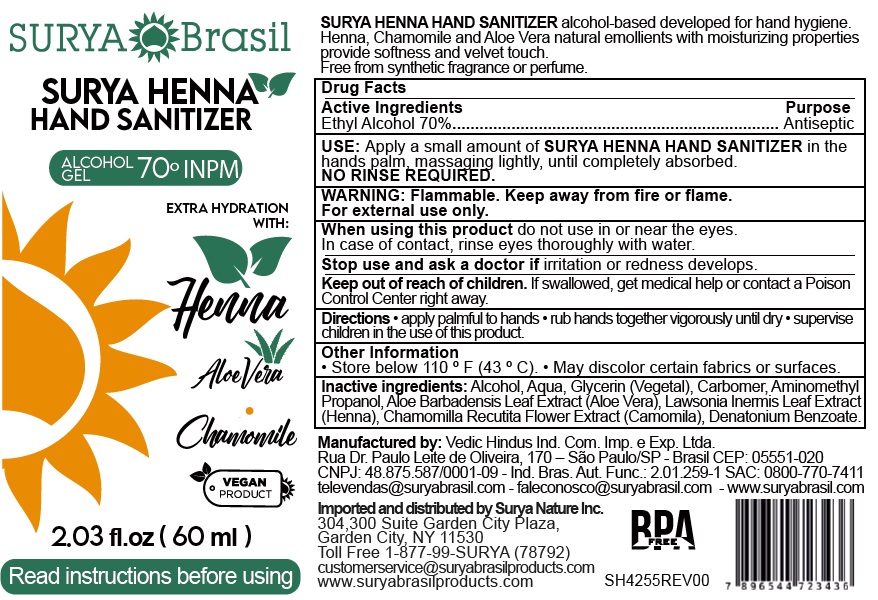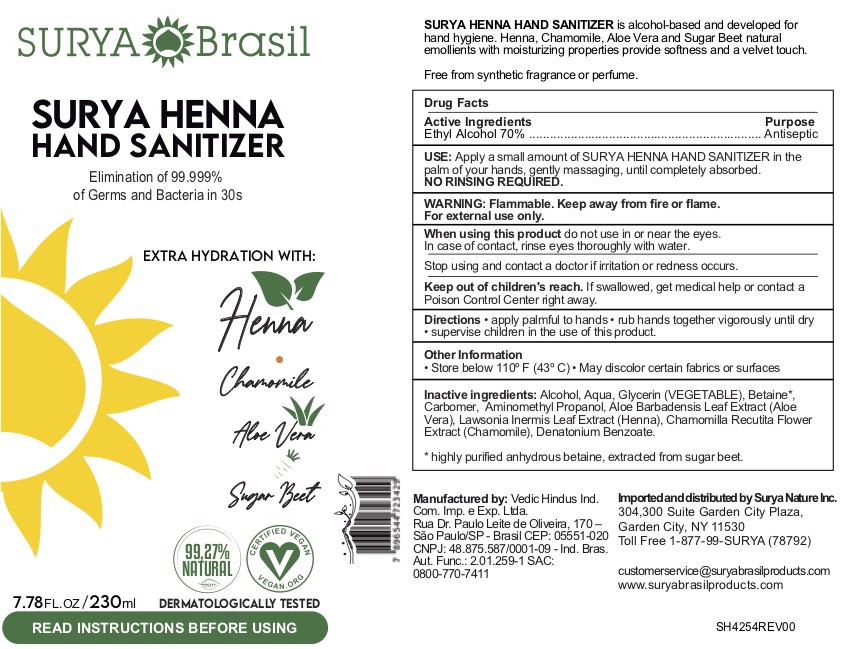 DRUG LABEL: Surya Henna Hand Sanitizer
NDC: 75252-720 | Form: GEL
Manufacturer: Surya Nature Inc
Category: otc | Type: HUMAN OTC DRUG LABEL
Date: 20201110

ACTIVE INGREDIENTS: ALCOHOL 70 mL/100 mL
INACTIVE INGREDIENTS: BETAINE; CARBOMER HOMOPOLYMER, UNSPECIFIED TYPE; AMINOMETHYLPROPANOL 0.15 mL/100 mL; CHAMOMILE 0.01 mL/100 mL; LAWSONIA INERMIS LEAF 0.01 mL/100 mL; DENATONIUM BENZOATE; GLYCERIN 2 mL/100 mL; WATER; ALOE VERA LEAF 0.02 mL/100 mL

This is a hand sanitizer manufactured according to the Temporary Policy for Preparation of Certain Alcohol-Based Hand Sanitizer Products During the Public Health Emergency (CoViD-19); Guidance for Industry.

The hand sanitizer is manufactured using only the following United States Pharmacopoeia (USP) grade ingredients in the preparation of the product (percentage in final product formulation) consistent with World Health Organization (WHO) recommendations:

1. Alcohol (ethanol) (USP or Food Chemical Codex (FCC) grade) (80%, volume/volume (v/v)) in an aqueous solution denatured according to Alcohol and Tobacco Tax and Trade Bureau regulations in 27 CFR part 20.
2. Glycerol (1.45% v/v).
3. Hydrogen peroxide (0.125% v/v).
4. Sterile distilled water or boiled cold water.

The firm does not add other active or inactive ingredients. Different or additional ingredients may impact the quality and potency of the product.

Active Ingredient(s)

Alcohol 70% v/v. Purpose: Antiseptic

Purpose

Antiseptic, Hand Sanitizer

Use

USE: Apply a small amount of SURYA HENNA HAND SANITIZER in the
hands palm, massaging lightly, until completely absorbed.
NO RINSE REQUIRED.

Warnings

Flammable. Keep away from fire or flame.
For external use only.

When using this product do not use in or near the eyes. In case of contact, rinse eyes thoroughly with water. Stop use and ask a doctor if irritation or rash appears and lasts Keep out of reach of children. If swallowed, get medical help or contact a Poison Control Center right away.

Do not use

When using this product do not use in or near the eyes.
In case of contact, rinse eyes thoroughly with water.

When using this product do not use in or near the eyes.In case of contact, rinse eyes thoroughly with water.
Stop use and ask a doctor if irritation or redness develops.
Keep out of reach of children. If swallowed, get medical help or contact a Poison Control Center right away.

Stop use and ask a doctor if irritation or redness develops.

Keep out of reach of children. If swallowed, get medical help or contact a Poison Control Center right away.

Directions

Directions • apply palmful to hands • rub hands together vigorously until dry
• supervise children in the use of this product.

Other information

  • Store below 110 º F (43 º C). • May discolor certain fabrics or surfaces.

Inactive ingredients

Inactive ingredients: Alcohol, Aqua, Glycerin (Vegetal), Carbomer, Aminomethyl
Propanol, Aloe Barbadensis Leaf Extract (Aloe Vera), Lawsonia Inermis Leaf Extract
(Henna), Chamomilla Recutita Flower Extract (Camomila), Denatonium Benzoate

Package Label - Principal Display Panel

230 mL NDC: 75252-720-10

60mL NDC: 75252-720-20